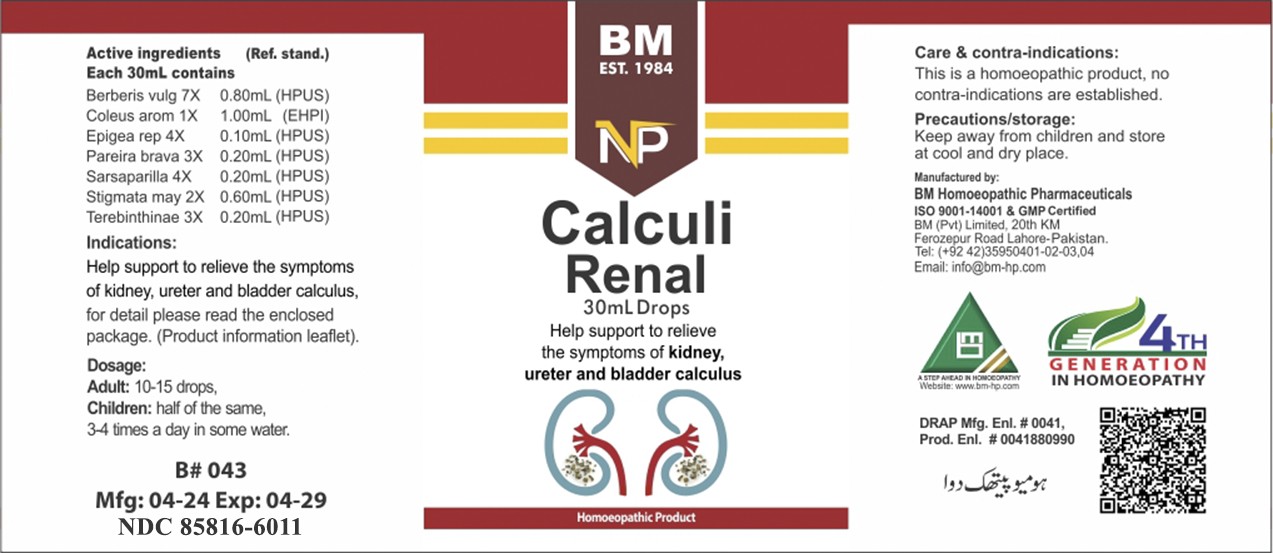 DRUG LABEL: CALCULI RENAL
NDC: 85816-6011 | Form: LIQUID
Manufacturer: BM Private Limited
Category: homeopathic | Type: HUMAN OTC DRUG LABEL
Date: 20250731

ACTIVE INGREDIENTS: TURPENTINE OIL 3 [hp_X]/1 mL; CHONDRODENDRON TOMENTOSUM ROOT 3 [hp_X]/1 mL; EPIGAEA REPENS 4 [hp_X]/1 mL; CORN SILK 2 [hp_X]/1 mL; COLEUS AMBOINICUS WHOLE 1 [hp_X]/1 mL; SARSAPARILLA 4 [hp_X]/1 mL; BERBERIS VULGARIS ROOT BARK 7 [hp_X]/1 mL
INACTIVE INGREDIENTS: ALCOHOL 0.96 mL/1 mL

BM HOMEOPATHIC LIQUID CALCULI RENAL

Dosage:
Adult:10-15 drops
Children: half of the same
3 times a day in some water

ACTIVE INGREDIENT

berberis vulg, coleus arom, epigea rep, pareira brava, sarsaparilla, stigmata may, terenbitinae

INACTIVE INGREDIENT

ALCOHOL

INDICATIONS AND USAGE

Help support to relieve the symptoms of kidney, ureter and bladder calculus,
for detail please read the enclosed package. (Product information leaflet).

PURPOSE

Help support to relieve the symptoms of kidney, ureter and bladder calculus,
for detail please read the enclosed package. (Product information leaflet).

CONTRAINDICATIONS

Care & contra-indications:
This is a homoeopathic remedy, no contra-indications are established.

WARNINGS

Precautions/storage:
Keep away from children and store at cool and dry place.

KEEP OUT OF REACH OF CHILDREN

Precautions/storage:
Keep away from children and store at cool and dry place.